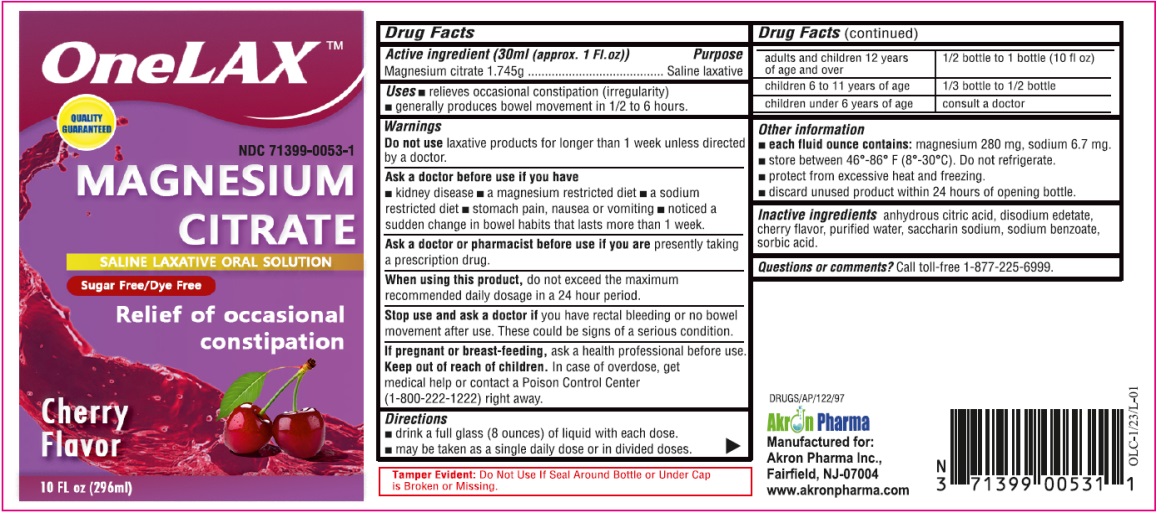 DRUG LABEL: OneLAX

NDC: 71399-0053 | Form: LIQUID
Manufacturer: AKRON PHARMA INC
Category: otc | Type: HUMAN OTC DRUG LABEL
Date: 20260112

ACTIVE INGREDIENTS: MAGNESIUM CITRATE 1.745 g/29.6 mL
INACTIVE INGREDIENTS: ANHYDROUS CITRIC ACID; EDETATE DISODIUM; WATER; SACCHARIN SODIUM; SODIUM BENZOATE; SORBIC ACID

OneLAX (Magnesium Citrate) Cherry
Sugar Free / Dye Free
Relief of occasional Constipation
Drug Facts

Active ingredient (30ml (approx. 1 Fl. oz))

Magnesium citrate 1.745g

Purpose

Saline laxative

Uses

- relieves occasional constipation (irregularity)
- generally produces bowel movement in 1/2 to 6 hours

Warnings

Do not use

laxative products for longer than 1 week unless directed by a doctor.

Ask a doctor before use if you have

- kidney disease
- a magnesium restricted diet
- a sodium restricted diet
- stomach pain, nausea or vomiting
- noticed a sudden change in bowel habits that lasts more than 1 week

Ask a doctor or pharmacist before use if you are

presently taking a prescription drug.

When using this product

do not exceed the maximum recommended daily dosage in a 24 hour period.

Stop use and ask a doctor if

you have rectal bleeding or no bowel movement after use. These could be signs of a serious condition.

If pregnant or breast-feeding,

ask a health professional before use.

Keep out of reach of children.

In case of overdose, get medical help or contact a Poison Control Center (1-800-222-1222) right away.

Directions

- drink a full glass (8 ounces) of liquid with each dose.
- may be taken as a single daily dose or in divided doses.

adults and children 12 years of age and over | 1/2 bottle to 1 bottle (10 fl oz)
children 6 to 11 years of age | 1/3 bottle to 1/2 bottle
children under 6 years of age | consult a doctor

Other information

- each fliud ounce contains:magnesium 280 mg, sodium 6.7 mg
- store between 46º-86ºF (8º-30ºC). Do not refrigerate.
- protect from excessive heat and freezing
- discard unused product within 24 hours of opening bottle

Inactive ingredients

citric acid, disodium edetate, cherry flavor, purified water, saccharin sodium, sodium benzoate, sorbic acid

Questions or comments?

Call toll-free 1-877-225-6999.

Manufactured for:

Akron Pharma Inc.,

Fairfield, NJ-07004

www.akronpharma.com